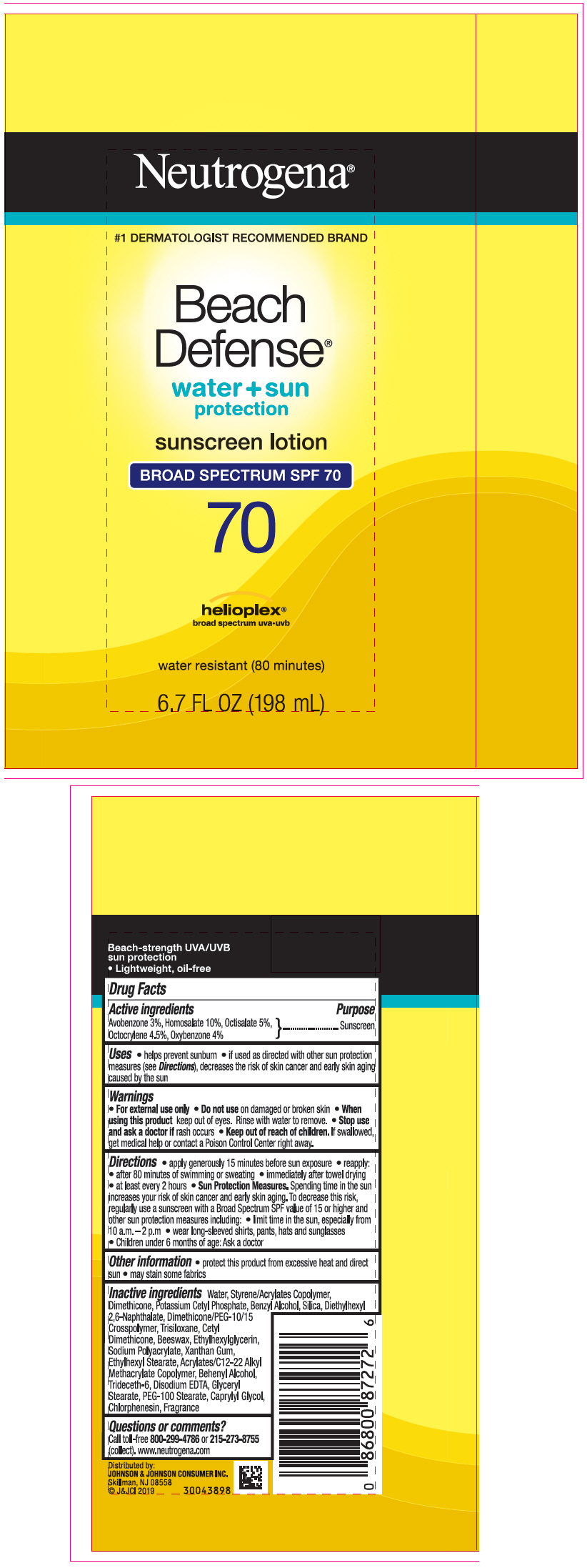 DRUG LABEL: Neutrogena Beach Defense Water Plus Sun Protection Sunscreen Broad Spectrum SPF 70
NDC: 69968-0560 | Form: LOTION
Manufacturer: Kenvue Brands LLC
Category: otc | Type: HUMAN OTC DRUG LABEL
Date: 20250908

ACTIVE INGREDIENTS: AVOBENZONE 30 mg/1 mL; HOMOSALATE 100 mg/1 mL; OCTISALATE 50 mg/1 mL; OCTOCRYLENE 45 mg/1 mL; OXYBENZONE 40 mg/1 mL
INACTIVE INGREDIENTS: BUTYL METHACRYLATE/METHYL METHACRYLATE/METHACRYLIC ACID/STYRENE CROSSPOLYMER; TRISILOXANE; BEESWAX; ETHYLHEXYLGLYCERIN; WATER; DIMETHICONE; POTASSIUM CETYL PHOSPHATE; BENZYL ALCOHOL; SILICA; DIETHYLHEXYL 2,6-NAPHTHALATE; XANTHAN GUM; ETHYLHEXYL STEARATE; BEHENYL ALCOHOL; TRIDECETH-6; EDETATE DISODIUM ANHYDROUS; GLYCERYL STEARATE; PEG-100 STEARATE; CAPRYLYL GLYCOL; CHLORPHENESIN; DIMETHICONE/PEG-10/15 CROSSPOLYMER; CETYL DIMETHICONE 25

Neutrogena® Beach Defense® water + sun protection sunscreen lotion BROAD SPECTRUM SPF 70

Drug Facts

ACTIVE INGREDIENT

Active ingredients | Purpose
Avobenzone 3% | Sunscreen
Homosalate 10% | Sunscreen
Octisalate 5% | Sunscreen
Octocrylene 4.5% | Sunscreen
Oxybenzone 4% | Sunscreen

Uses

- helps prevent sunburn
- if used as directed with other sun protection measures (see Directions), decreases the risk of skin cancer and early skin aging caused by the sun

Warnings

- For external use only

- Do not use on damaged or broken skin

- When using this product keep out of eyes. Rinse with water to remove.

- Stop use and ask a doctor if rash occurs

- Keep out of reach of children. If swallowed, get medical help or contact a Poison Control Center right away.

Directions

For Sunscreen Use:

- apply generously 15 minutes before sun exposure
- reapply:
  - after 80 minutes of swimming or sweating
  - immediately after towel drying
  - at least every 2 hours
- Sun Protection Measures. Spending time in the sun increases your risk of skin cancer and early skin aging. To decrease this risk, regularly use a sunscreen with a Broad Spectrum SPF value of 15 or higher and other sun protection measures including:
  - limit time in the sun, especially from 10 a.m. - 2 p.m.
  - wear long-sleeved shirts, pants, hats and sunglasses
  - Children under 6 months of age: Ask a doctor

Other information

- protect this product from excessive heat and direct sun
- may stain some fabrics

Inactive ingredients

Water, Styrene/Acrylates Copolymer, Dimethicone, Potassium Cetyl Phosphate, Benzyl Alcohol, Silica, Diethylhexyl 2,6-Naphthalate, Dimethicone/PEG-10/15 Crosspolymer, Trisiloxane, Cetyl Dimethicone, Beeswax, Ethylhexylglycerin, Sodium Polyacrylate, Xanthan Gum, Ethylhexyl Stearate, Acrylates/C12-22 Alkyl Methacrylate Copolymer, Behenyl Alcohol, Trideceth-6, Disodium EDTA, Glyceryl Stearate, PEG-100 Stearate, Caprylyl Glycol, Chlorphenesin, Fragrance

Questions or Comments?

Call toll-free 800-299-4786 or 215-273-8755 (collect). www.neutrogena.com

Distributed by:
JOHNSON & JOHNSON CONSUMER INC.
Skillman, NJ 08558

PRINCIPAL DISPLAY PANEL - 198 mL Bottle Label

Neutrogena®

#1 DERMATOLOGIST RECOMMENDED BRAND

Beach
Defense®
water + sun
protection

sunscreen lotion
BROAD SPECTRUM SPF 70

70

helioplex®
broad spectrum uva•uvb

water resistant (80 minutes)

6.7 FL OZ (198 mL)